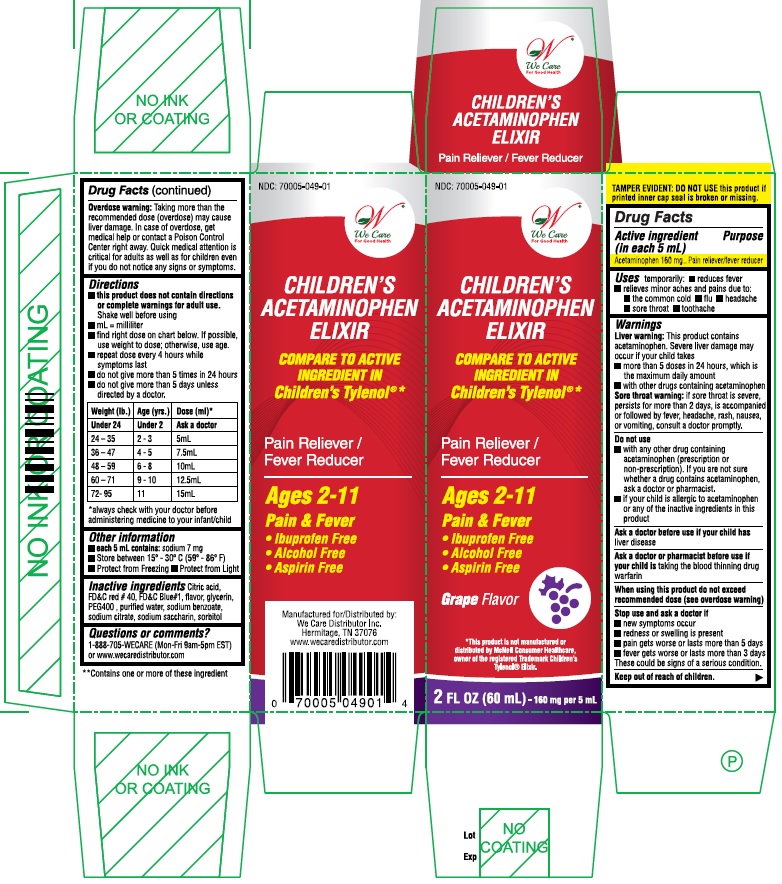 DRUG LABEL: Childrens Acetaminophen
NDC: 70005-049 | Form: ELIXIR
Manufacturer: We Care Distributor Inc.
Category: otc | Type: HUMAN OTC DRUG LABEL
Date: 20161013

ACTIVE INGREDIENTS: Acetaminophen 160 mg/5 mL
INACTIVE INGREDIENTS: ANHYDROUS CITRIC ACID; FD&C RED NO. 40; FD&C BLUE NO. 1; GLYCERIN; POLYETHYLENE GLYCOL 400; SODIUM BENZOATE; SODIUM CITRATE; SACCHARIN SODIUM; SORBITOL; WATER

Drug Facts

Active ingredient (in each 5 mL)

Acetaminophen 160 mg

Purpose

Pain reliever/Fever reducer

Uses

temporarily:

- reduces fever
- relieves minor aches and pains due to:
- the common cold
- flu
- headache
- sore throat
- toothache

Warnings

Liver warning:

This product contains acetaminophen. Severe liver damage may occur if your child takes

- more than 5 doses in 24 hours, which is the maximum daily amount
- with other drugs containing acetaminophen

Sore throat warning

if sore throat is severe, persists for more than 2 days, is accompanied or followed by fever, headache, rash, nausea, or vomiting, consult a doctor promptly.

Do not use

- with any other drug containing acetaminophen (prescription or non-prescription). If you are not sure whether a drug contains acetaminophen, ask a doctor or pharmacist.
- if your child is allergic to acetaminophen or any of the inactive ingredients in this product

Ask a doctor before use if your child has liver disease

Ask a doctor or pharmacist before use if your child is taking the blood thinning drug warfarin

When using this product do not exceed recommended dose (see overdose warning)

Stop use and ask a doctor if

- new symptoms occur
- redness or swelling is present
- pain gets worse or lasts more than 5 days
- fever gets worse or lasts more than 3 days

These could be signs of a serious condition.

Keep out of reach of children.

Overdose warning

Taking more than the recommended dose (overdose) may cause liver damage. In case of overdose, get medical help or contact a Poison Control Center right away. Quick medical attention is critical for adults as well as for children even if you do not notice any signs or symptoms.

Directions

- this product does not contain directions or complete warnings for adult use.
- shake well before using
- mL = milliliter
- find right dose on chart below. If possible, use weight to dose; otherwise, use age.
- repeat dose every 4 hours while symptoms last
- do not give more than 5 times in 24 hours
- do not give more than 5 days unless directed by a doctor

Weight (lb.) Age(yrs.) Dose (mL*)

Under 24 Under 2 Ask a doctor

24-35 2-3 5 mL

36-47 4-5 7.5 mL

48-59 6-8 10 mL

60-71 9-10 12.5 mL

72-95 11 15 mL

* always check with your doctor before administering medicine to your infant/child

Other information

- each teaspoon (5 mL) contains: sodium 7 mg
- Store at room temperature 15º - 30ºC (59º - 86ºF)
- Protect from Freezing.
- Protect from Light.
- TAMPER EVIDENT: DO NOT USE THIS PRODUCT IF PRINTED INNER CAP SEAL IS BROKEN OR MISSING

Inactive ingredients

citric acid, FD&C red # 40, FD&C blue # 1, flavor, glycerin. PEG 400, purified water, sodium benzoate, sodium citrate, sodium saccharin, sorbitol

QUESTIONS OR COMMENTS

1-888-705-WECARE (Mon-Fri 9am-5pm EST) or www.wecaredistributor.com

PRINCIPAL DISPLAY PANEL

*Compare to the active ingredient in Children's Tylenol® Elixir

Children's Acetaminophen Elixir
Grape Flavor
For ages 2 to 11
2 FL OZ (60 mL)